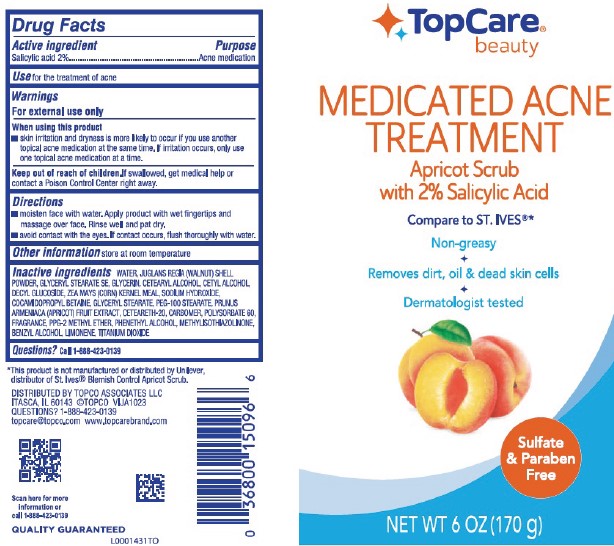 DRUG LABEL: Medicated Apricot Scrub
NDC: 36800-009 | Form: GEL
Manufacturer: Topco Associates LLC
Category: otc | Type: HUMAN OTC DRUG LABEL
Date: 20260213

ACTIVE INGREDIENTS: SALICYLIC ACID 20 mg/1 g
INACTIVE INGREDIENTS: JUGLANS REGIA SHELL; GLYCERYL STEARATE SE; GLYCERIN; CETYL ALCOHOL; DECYL GLUCOSIDE; CORN GRAIN; SODIUM HYDROXIDE; COCAMIDOPROPYL BETAINE; GLYCERYL MONOSTEARATE; PEG-100 STEARATE; APRICOT; POLYOXYL 20 CETOSTEARYL ETHER; CARBOMER HOMOPOLYMER, UNSPECIFIED TYPE; POLYSORBATE 60; PPG-2 METHYL ETHER; PHENYLETHYL ALCOHOL; METHYLISOTHIAZOLINONE; BENZYL ALCOHOL; LIMONENE, (+)-; WATER; TITANIUM DIOXIDE

Top Care 041.006/041AK rev 0
Medicated Apricot Scrub

Active ingredient

Salicylic acid 2%

Purpose

Acne medication

Use

for the treatment of acne

Warnings

For external use only

When using this product

- skin irritation and dryness is more likely to occur if you use another topical acne medication at the same time. If irritation occurs, only use one topical acne medication at a time.

Keep out of reach of children.

If swallowed, get medical help or contact a Poison Control Center right away.

Directions

- moisten face with water. Apply product with wet fingertips and massage over face. Rinse well and pat dry.
- avoid contact with eyes. If contact occurs, flush thoroughly with water.

Other information

Store at room temperature

Inactive ingredients

water, Juglans regia (walnut) shell powder, glyceryl stearate SE, glycerin, cetearyl alcohol, cetyl alcohol, decyl glucoside, Zea mays (corn) kernel meal, sodium hydroxide, cocamidopropyl betaine, glyceryl stearate, PEG-100 stearate, Prunus armeniaca (apricot) fruit extract, ceteareth-20, carbomer, polysorbate 60, fragrance, PPG-2 methyl ether, phenethyl alcohol, methylisothiazolinone, benzyl alcohol, limonene, titanium dioxide

Questions?

Call 1-888-423-0139

Disclaimer

*This product is not manufactured or distributed by Unilever, distributor of St. Ives®Blemish Control Apricot Scrub.

Adverse reaction

DISTRIBUTED BY TOPCO ASSOCIATES LLC

ITASCA, IL 60143 ©TOPCO VIJ 1023

QUESTIONS? 1-888-423-0139

topcare@topco.com www.topcarebrand.com

Scan here for more information or call 1-888-423-0139

QUALITY GUARANTEED

Principal display panel

TopCare®

beauty

MEDICATED ACNE TREATMENT

Apricot Scrub

with 2% Salicylic Acid

Compare to ST. IVES®*

Non-greasy

Removes dirt, oil & dead skin cells

Dermatologist tested

Sulfate & Paraben Free

NET WT 6 OZ (170 g)